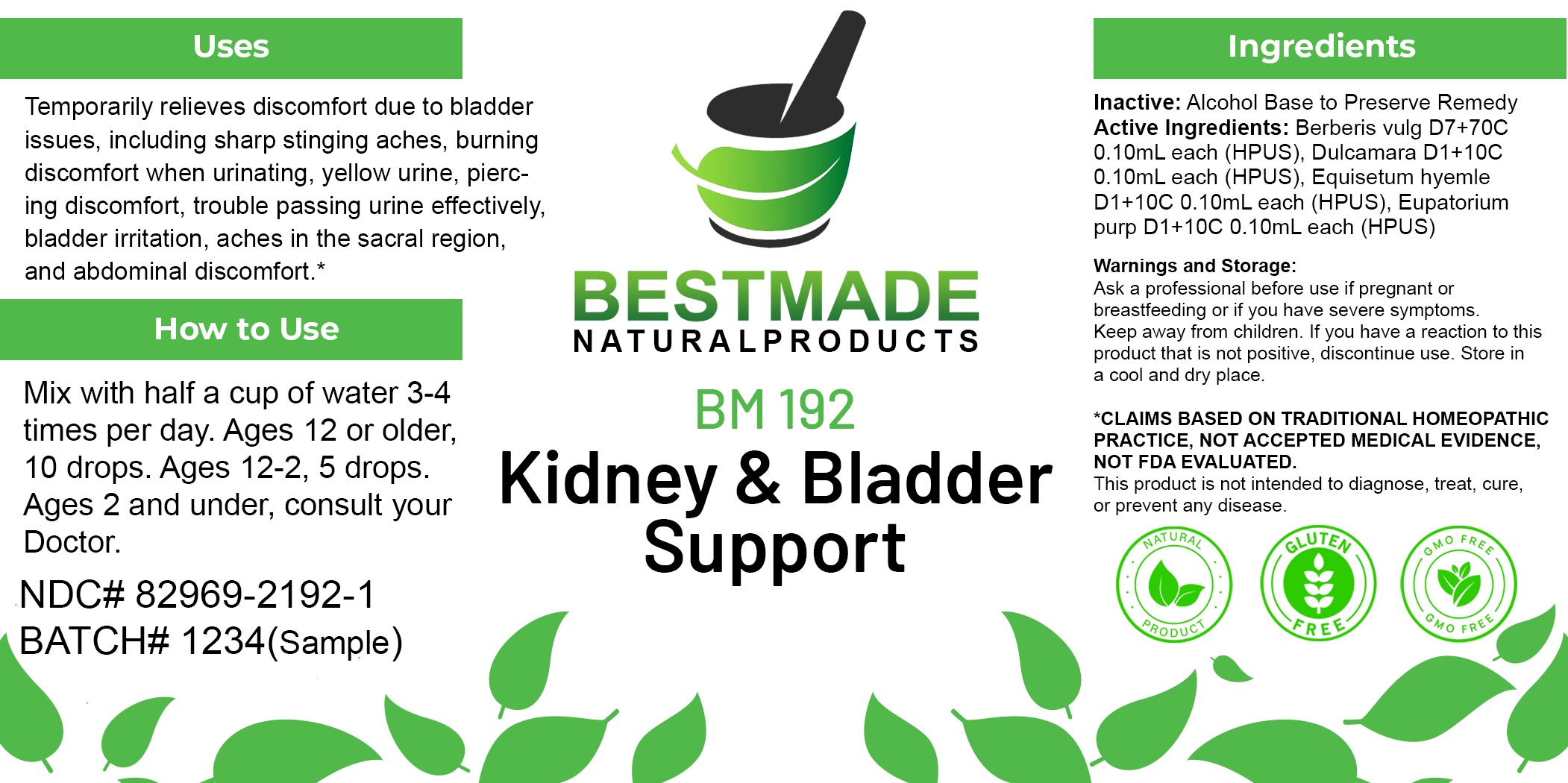 DRUG LABEL: Bestmade Natural Products BM192
NDC: 82969-2192 | Form: LIQUID
Manufacturer: Bestmade Natural Products
Category: homeopathic | Type: HUMAN OTC DRUG LABEL
Date: 20250221

ACTIVE INGREDIENTS: SOLANUM DULCAMARA TOP 30 [hp_C]/30 [hp_C]; BERBERIS VULGARIS ROOT BARK 30 [hp_C]/30 [hp_C]; EUTROCHIUM PURPUREUM ROOT 30 [hp_C]/30 [hp_C]; EQUISETUM HYEMALE 30 [hp_C]/30 [hp_C]
INACTIVE INGREDIENTS: ALCOHOL 30 [hp_C]/30 [hp_C]

BM192

DOSAGE AND ADMINISTRATION

How to Use

Mix with half a cup of water 3-4 times per day. Ages 12 or older, 10 drops. Ages 12-2, 5 drops. Ages 2 and under, consult your Doctor.

Inactive:

Alcohol Base to Preserve Product

ACTIVE INGREDIENT

Active Ingredients: Berberis vulg D7+70C 0.10mL each (HPUS), Dulcamara D1+10C 0.10mL each (HPUS), Equisetum hyemle D1+10C 0.10mL each (HPUS), Eupatorium purp D1+10C 0.10mL each (HPUS)

KEEP OUT OF REACH OF CHILDREN

Warnings and Storage:

Ask a professional before use if pregnant or breastfeeding or if you have severe symptoms.

Keep away from children. If you have a reaction to this product that is not positive, discontinue use. Store in a cool and dry place

*CLAIMS BASED ON TRADITIONAL HOMEOPATHIC PRACTICE, NOT ACCEPTED MEDICAL EVIDENCE NOT FDA EVALUATED.
This product is not intended to diagnose, treat, cure, or prevent any disease.

Warnings and Storage:

Ask a professional before use if pregnant or breastfeeding or if you have severe symptoms.

Keep away from children. If you have a reaction to this product that is not positive, discontinue use. Store in a cool and dry place

*CLAIMS BASED ON TRADITIONAL HOMEOPATHIC PRACTICE, NOT ACCEPTED MEDICAL EVIDENCE NOT FDA EVALUATED.
This product is not intended to diagnose, treat, cure, or prevent any disease.

Uses
Temporarily relieves discomfort due to bladder issues, including sharp stinging aches, burning discomfort when urinating, yellow urine, piercing discomfort, trouble passing urine effectively, bladder irritation, aches in the sacral region, and abdominal discomfort.*

Uses
Temporarily relieves discomfort due to bladder issues, including sharp stinging aches, burning discomfort when urinating, yellow urine, piercing discomfort, trouble passing urine effectively, bladder irritation, aches in the sacral region, and abdominal discomfort.*

Entire package label